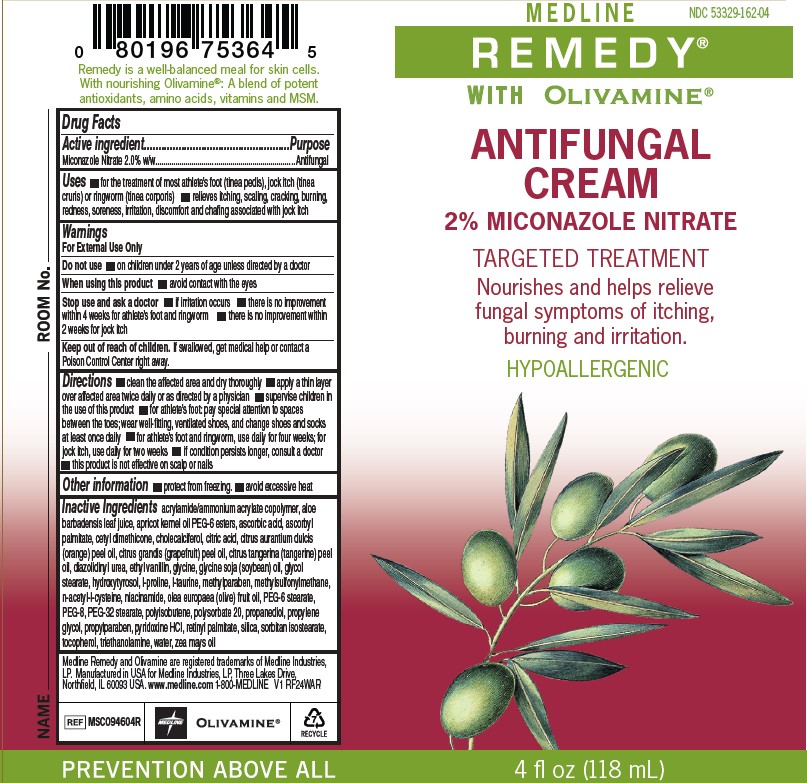 DRUG LABEL: Remedy Antifungal
NDC: 53329-162 | Form: CREAM
Manufacturer: Medline Industries, LP
Category: otc | Type: HUMAN OTC DRUG LABEL
Date: 20251028

ACTIVE INGREDIENTS: MICONAZOLE NITRATE 2 g/100 g
INACTIVE INGREDIENTS: CETYL DIMETHICONE 25; SORBITAN ISOSTEARATE; TROLAMINE; CORN OIL; POLYISOBUTYLENE (1000 MW); CHOLECALCIFEROL; PYRIDOXINE HYDROCHLORIDE; TOCOPHEROL; HYDROXYTYROSOL; PROPYLENE GLYCOL; TAURINE; NIACINAMIDE; POLYSORBATE 20; ACRYLAMIDE; METHYLPARABEN; DIMETHYL SULFONE; PROPYLPARABEN; VITAMIN A PALMITATE; APRICOT KERNEL OIL PEG-6 ESTERS; ETHYL VANILLIN; PROPANEDIOL; ALOE VERA LEAF; ACETYLCYSTEINE; SILICON DIOXIDE; WATER; ASCORBIC ACID; ORANGE OIL; ASCORBYL PALMITATE; OLIVE OIL; PEG-32 STEARATE; CITRIC ACID MONOHYDRATE; CITRUS MAXIMA FRUIT RIND OIL; MANDARIN OIL; PEG-6 STEARATE; POLYETHYLENE GLYCOL 400; DIAZOLIDINYL UREA; SOYBEAN OIL; PROLINE; GLYCINE; GLYCOL STEARATE

162 Antifungal Cream 2% Miconazole Nitrate

Active ingredient

Miconazole Nitrate 2.0% w/w

Purpose

Antifungal

Use

- For the treatment of most athlete’s foot (tinea pedis), jock itch (tinea cruris), ringworm (tinea corporis)
- Relieves itching, scaling, cracking, burning, redness, soreness, irritation, discomfort and chafing associated with jock itch

Warnings

For external use only

Do not use

- on children under 2 years of age unless directed by a doctor

When using this product

- avoid contact with the eyes

Stop use and ask a doctor

- if irritation occurs
- there is no improvement within 4 weeks for athlete’s foot and ringworm
- there is no improvement within 2 weeks for jock itch

Keep out of reach of children.

If swallowed, get medical help or contact a Poison Control Center right away.

Directions

- clean the affected area and dry thoroughly
- apply a thin layer over affected area twice daily or as directed by a physician
- supervise children in the use of this product
- for athlete’s foot: pay special attention to spaces between the toes: wear well-fitting, ventilated shoes, and change shoes and socks at least once daily
- for athlete’s foot and ringworm, use daily for four weeks; for jock itch, use daily for two weeks
- if condition persists longer, consult a doctor
- this product is not effective on the scalp or nails

Other information

- Protect from freezing. Avoid excessive heat.

Inactive ingredients

acrylamide/ammonium acrylate copolymer, aloe barbadensis leaf juice, apricot kernel oil PEG-6 esters, ascorbic acid, ascorbyl palmitate, cetyl dimethicone, cholecalciferol, citric acid, citrus aurantium dulcis (orange) peel oil, citrus grandis (grapefruit) peel oil, citrus tangerina (tangerine) peel oil, diazolidinyl urea, ethyl vanillin, glycine, glycine soja (soybean) oil, glycol stearate, hydroxytyrosol, l-proline, l-taurine, methylparaben, methylsulfonylmethane, n-acetyl-l-cysteine, niacinamide, olea europaea (olive) fruit oil, PEG-6 stearate, PEG-8, PEG-32 stearate, polyisobutene, polysorbate 20, propanediol, propylene glycol, propylparaben, pyridoxine HCI, retinyl palmitate, silica, sorbitan isostearate, tocopherol, triethanolamine, water, zea mays oil

Medline Remedy and Olivamine are registered trademarks of Medline Industries, LP. Manufactured in USA for Medline Industries, LP, Three Lakes Drive, Northfield, IL 60093 USA.
www.medline.com 1-800-MEDLINE

RECENT MAJOR CHANGES

update to directions to reflect current labeling.